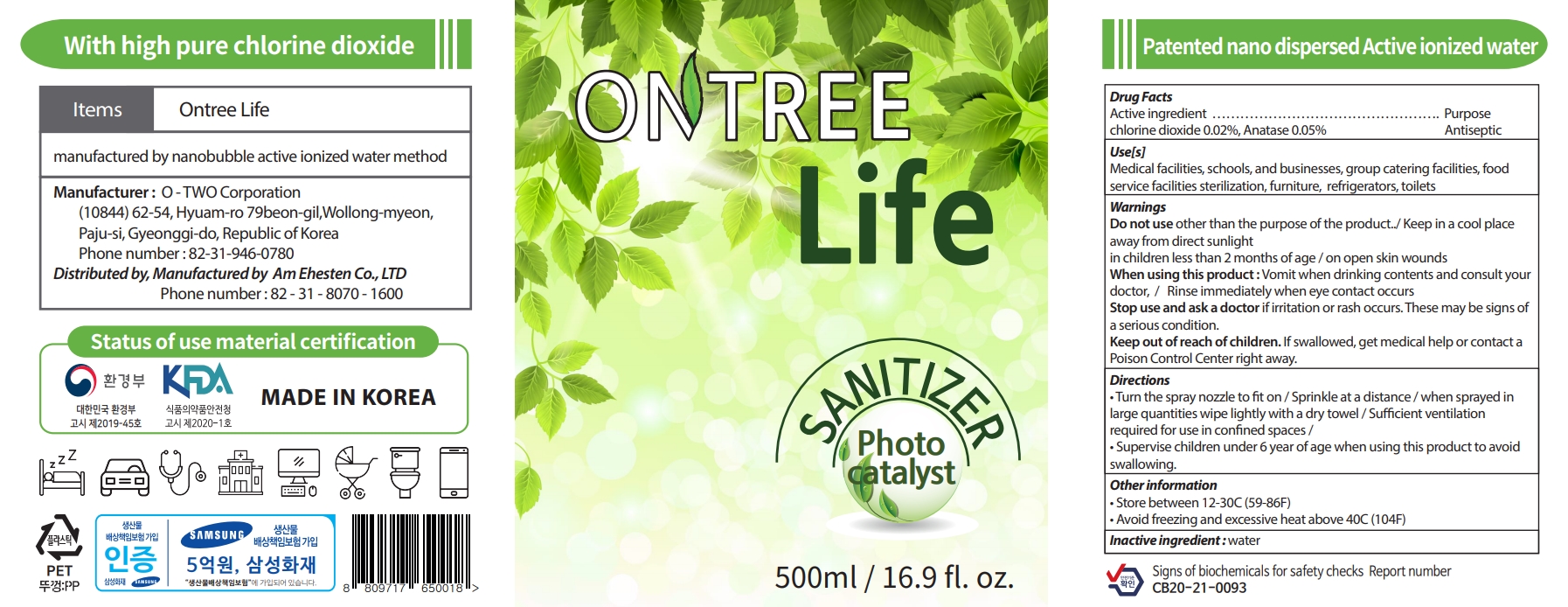 DRUG LABEL: ONTREE LIFE
NDC: 90105-202 | Form: LIQUID
Manufacturer: O2
Category: otc | Type: HUMAN OTC DRUG LABEL
Date: 20200904

ACTIVE INGREDIENTS: CHLORINE DIOXIDE 0.02 g/100 mL; TITANIUM DIOXIDE 0.05 g/100 mL
INACTIVE INGREDIENTS: WATER

90105-202

Active ingredient

Chlorine dioxide 0.02%

Anatase 0.05%

Purpose

Antiseptic

Use

Medical facilities, schools, and businesses, group catering facilities, food service facilities sterilization, furniture, refrigerators, toilets

Warnings

Do not use other than the purpose of the product../ Keep in a cool place away from direct sunlight in children less than 2 months of age / on open skin wounds

When using this product : Vomit when drinking contents and consult your doctor, / Rinse immediately when eye contact occurs

Stop use and ask a doctor

if irritation or rash occurs. These may be signs of a serious condition.

Keep out of reach of children.

If swallowed, get medical help or contact a Poison Control Center right away.

Directions

• Turn the spray nozzle to fit on / Sprinkle at a distance / when sprayed in large quantities wipe lightly with a dry towel / Sufficient ventilation required for use in confined spaces /

• Supervise children under 6 year of age when using this product to avoid swallowing.

Other information

• Store between 12-30C (59-86F)

• Avoid freezing and excessive heat above 40C (104F)

Inactive ingredient

water